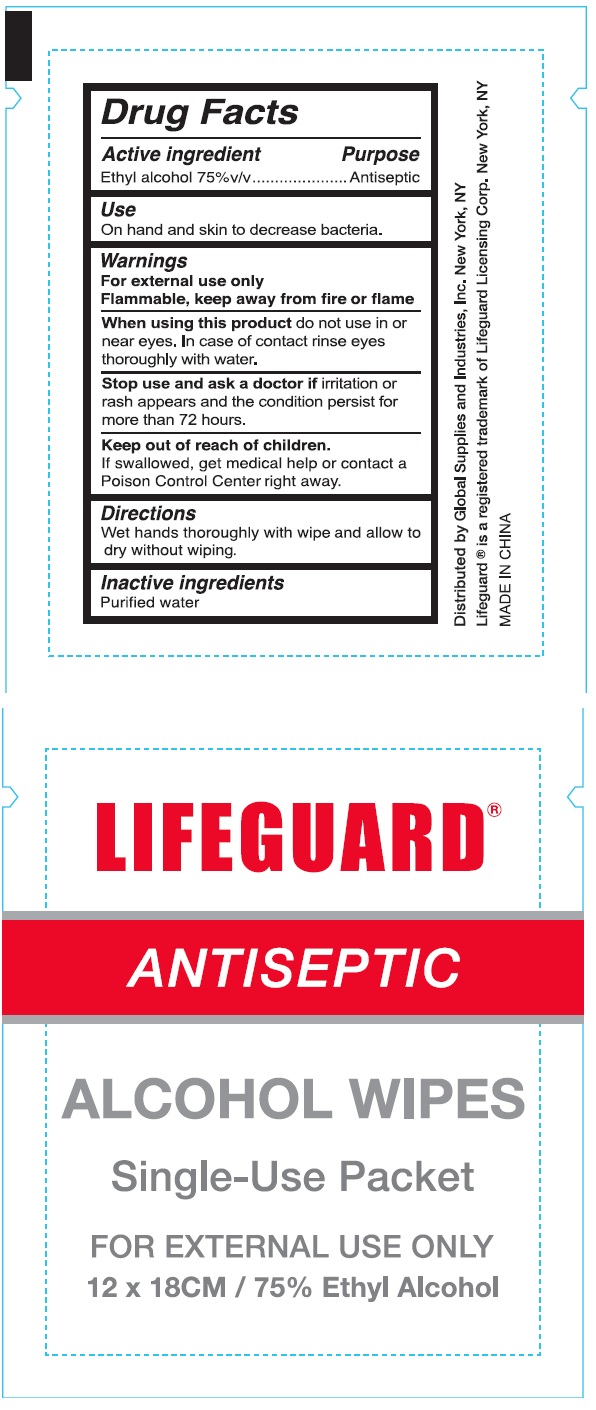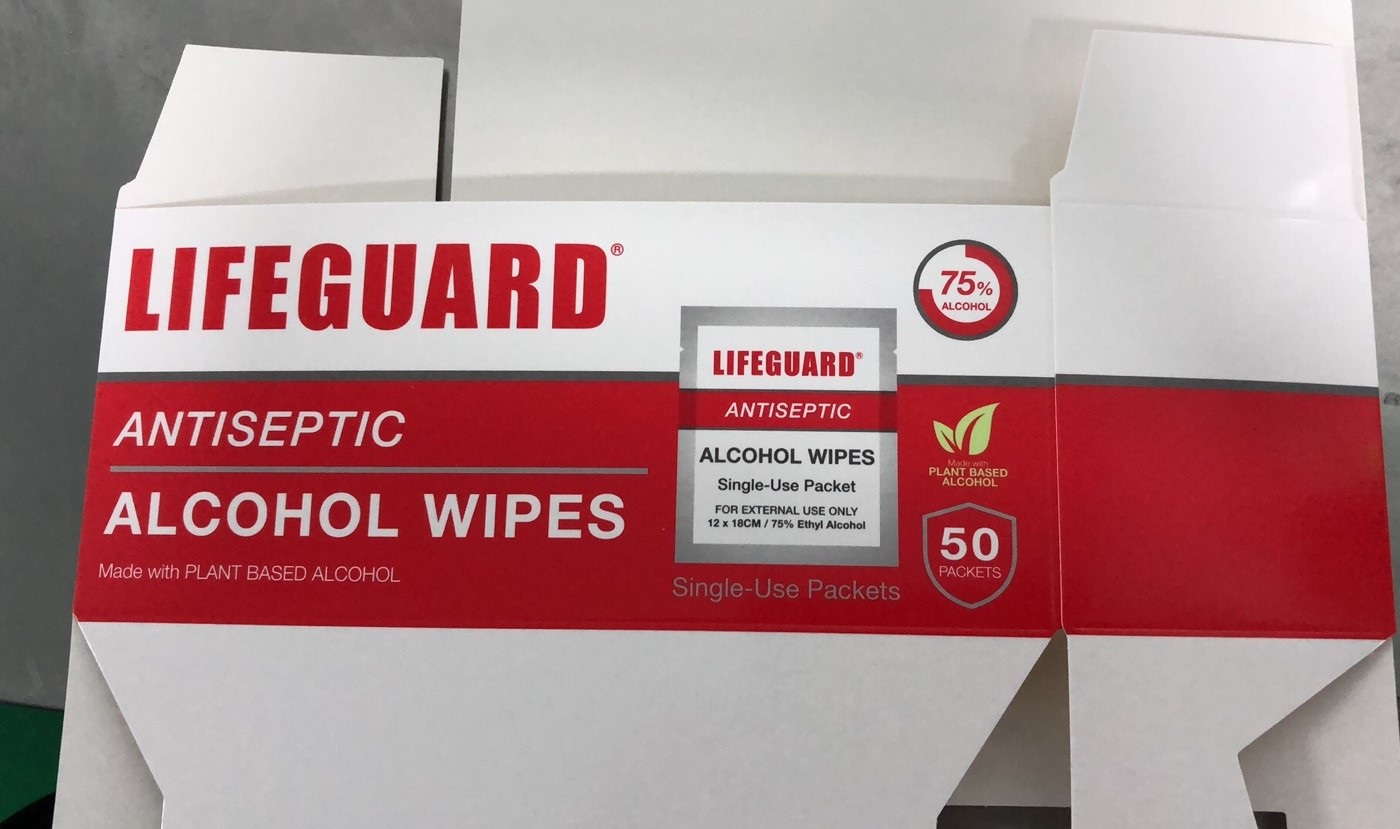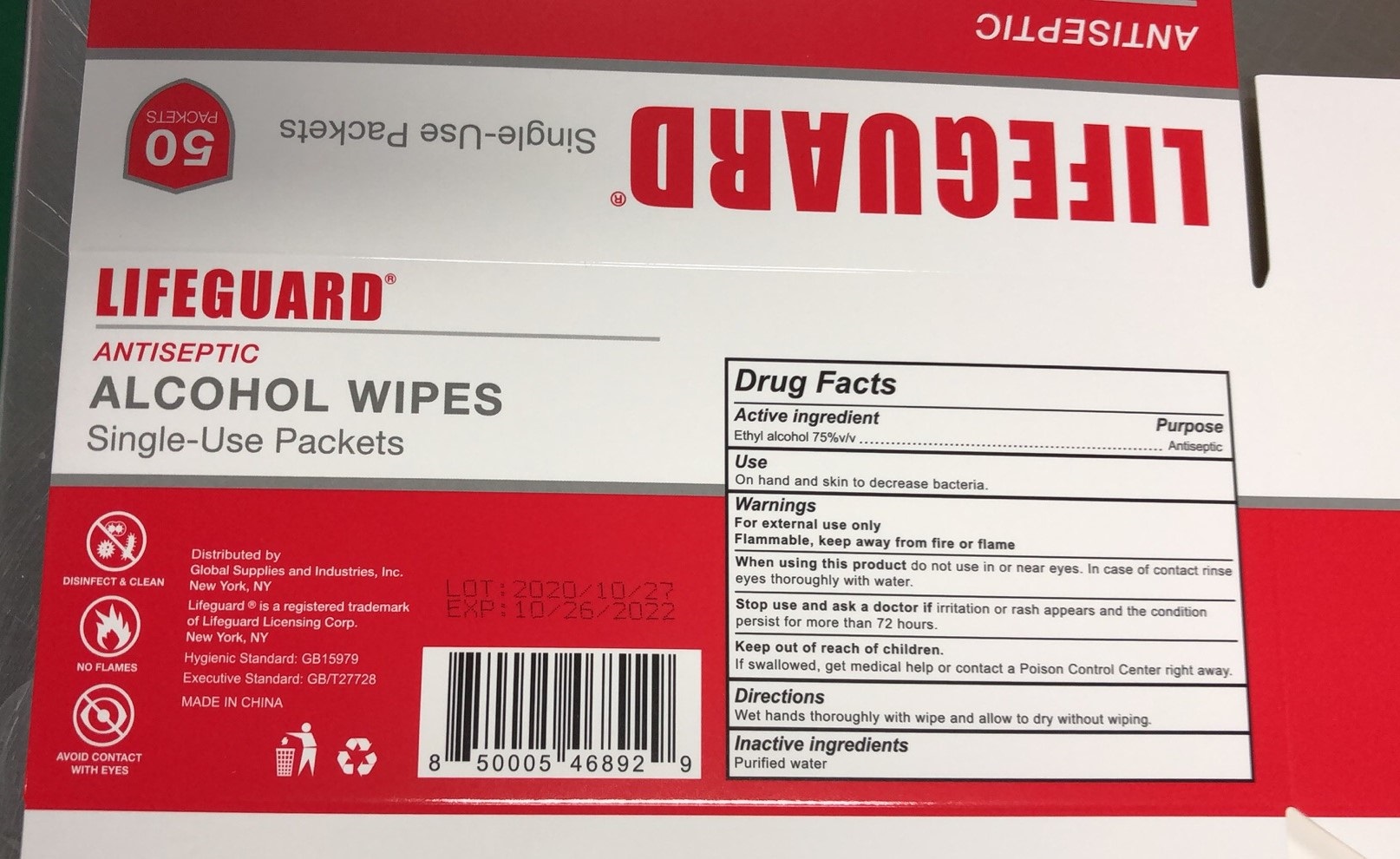 DRUG LABEL: LFG-IND-WIPES Single Use Alcohol Wipe Packets
NDC: 77879-005 | Form: LIQUID
Manufacturer: BT Supplies West Inc
Category: otc | Type: HUMAN OTC DRUG LABEL
Date: 20220209

ACTIVE INGREDIENTS: ALCOHOL 0.75 mL/1 mL
INACTIVE INGREDIENTS: WATER

LFG-IND-WIPES Single Use Alcohol Wipe Packets

Active ingredient

Ethyl alcohol 70% v/v

Purpose

Antiseptic

Uses

On hand and skin to decrease bacteria.

Warnings

For external use only
Flammable, Keep away from fire or flame

When using this product

do not use in or near eyes. In case of contact rinse eyes thoroughly with water.

Stop use and ask a doctor if

irritation or rash appears and lasts and condition persist for more than 72 hours.

Keep out of reach of children.

If swallowed, get medical help or contact a Poison Control Center right away.

Directions

Wet hands thoroughly with wipe and allow to dry without wiping.

Inactive ingredients

Purified water